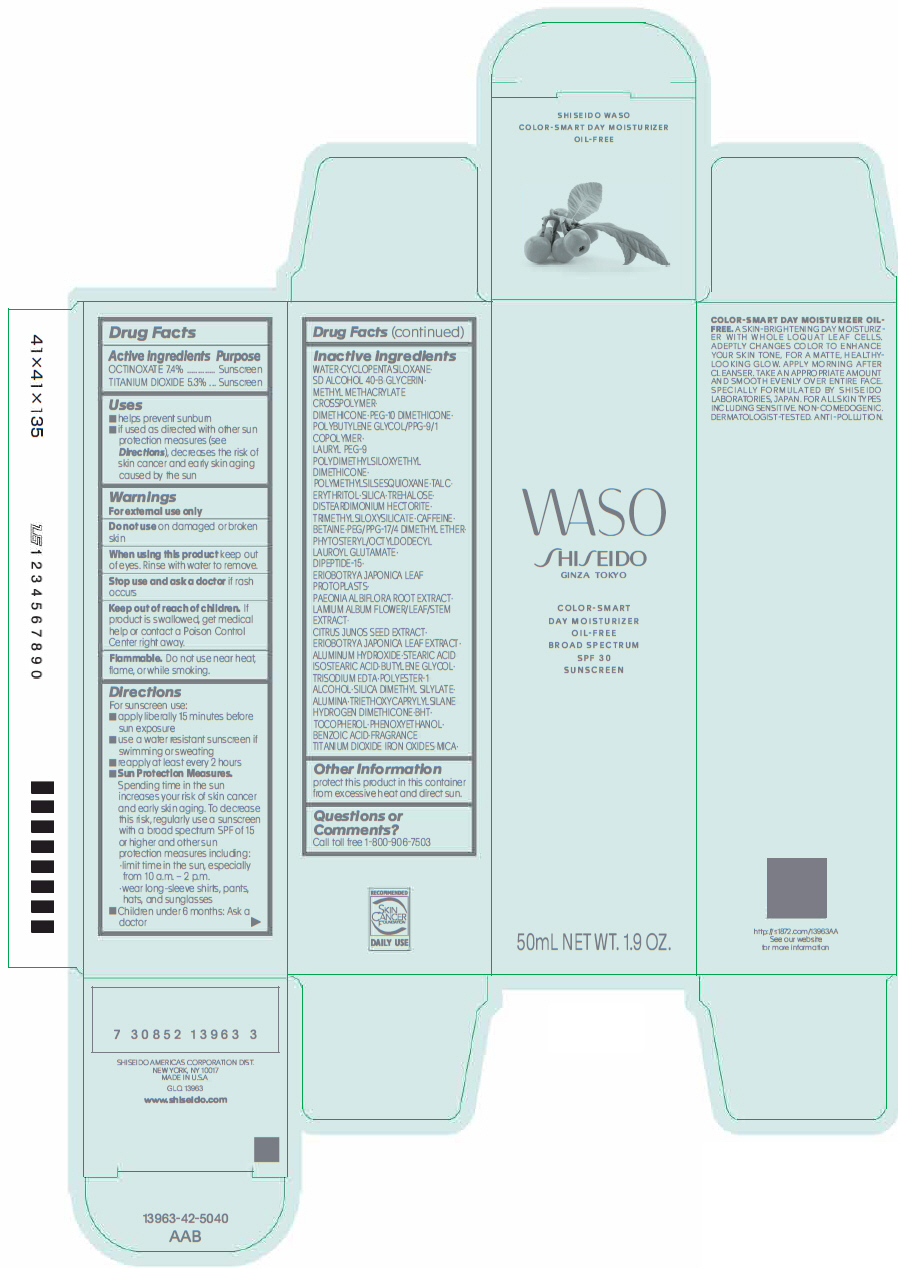 DRUG LABEL: shiseido waso color-smart day moisturizer oil-free
NDC: 58411-457 | Form: EMULSION
Manufacturer: SHISEIDO AMERICAS CORPORATION
Category: otc | Type: HUMAN OTC DRUG LABEL
Date: 20181127

ACTIVE INGREDIENTS: OCTINOXATE 4177 mg/50 mL; TITANIUM DIOXIDE 2992 mg/50 mL
INACTIVE INGREDIENTS: WATER; CYCLOMETHICONE 5; GLYCERIN; METHYL METHACRYLATE/GLYCOL DIMETHACRYLATE CROSSPOLYMER; DIMETHICONE; PEG-10 DIMETHICONE (600 CST); LAURYL PEG-9 POLYDIMETHYLSILOXYETHYL DIMETHICONE; POLYMETHYLSILSESQUIOXANE (4.5 MICRONS); TALC; ERYTHRITOL; SILICON DIOXIDE; TREHALOSE; DISTEARDIMONIUM HECTORITE; TRIMETHYLSILOXYSILICATE (M/Q 0.6-0.8); CAFFEINE; BETAINE; PEG/PPG-17/4 DIMETHYL ETHER; PHYTOSTERYL/OCTYLDODECYL LAUROYL GLUTAMATE; DIGLYCINE; PAEONIA LACTIFLORA ROOT; LAMIUM ALBUM FLOWERING TOP; CITRUS JUNOS SEED; ALUMINUM HYDROXIDE; STEARIC ACID; ISOSTEARIC ACID; BUTYLENE GLYCOL; EDETATE TRISODIUM; ALCOHOL; SILICA DIMETHYL SILYLATE; ALUMINUM OXIDE; TRIETHOXYCAPRYLYLSILANE; HYDROGEN DIMETHICONE (13 CST); BUTYLATED HYDROXYTOLUENE; .ALPHA.-TOCOPHEROL; PHENOXYETHANOL; BENZOIC ACID; FERRIC OXIDE RED; FERRIC OXIDE YELLOW; FERROSOFERRIC OXIDE; MICA

SHISEIDO WASO COLOR-SMART DAY MOISTURIZER OIL-FREE

Drug Facts

ACTIVE INGREDIENT

Active ingredients | Purpose
OCTINOXATE 7.4% | Sunscreen
TITANIUM DIOXIDE 5.3% | Sunscreen

Uses

- helps prevent sunburn
- if used as directed with other sun protection measures (see Directions), decreases the risk of skin cancer and early skin aging caused by the sun

Warnings

For external use only

Do not use on damaged or broken skin

When using this product keep out of eyes. Rinse with water to remove.

Stop use and ask a doctor if rash occurs

Keep out of reach of children. If product is swallowed, get medical help or contact a Poison Control Center right away.

Flammable. Do not use near heat, flame, or while smoking.

Directions

For sunscreen use:

- apply liberally 15 minutes before sun exposure
- use a water resistant sunscreen if swimming or sweating
- reapply at least every 2 hours
- Sun Protection Measures. Spending time in the sun increases your risk of skin cancer and early skin aging. To decrease this risk, regularly use a sunscreen with a broad spectrum SPF of 15 or higher and other sun protection measures including:
  - limit time in the sun, especially from 10 a.m. – 2 p.m.
  - wear long-sleeve shirts, pants, hats, and sunglasses
- Children under 6 months: Ask a doctor

Inactive Ingredients

WATER∙CYCLOPENTASILOXANE∙SD ALCOHOL 40-B GLYCERIN∙METHYL METHACRYLATE CROSSPOLYMER∙DIMETHICONE∙PEG-10 DIMETHICONE∙POLYBUTYLENE GLYCOL/PPG-9/1 COPOLYMER∙LAURYL PEG-9 POLYDIMETHYLSILOXYETHYL DIMETHICONE∙POLYMETHYLSILSESQUIOXANE∙TALC∙ERYTHRITOL∙SILICA∙TREHALOSE∙DISTEARDIMONIUM HECTORITE∙TRIMETHYLSILOXYSILICATE∙CAFFEINE∙BETAINE∙PEG/PPG-17/4 DIMETHYL ETHER∙PHYTOSTERYL/OCTYLDODECYL LAUROYL GLUTAMATE∙DIPEPTIDE-15∙ERIOBOTRYA JAPONICA LEAF PROTOPLASTS∙PAEONIA ALBIFLORA ROOT EXTRACT∙LAMIUM ALBUM FLOWER/LEAF/STEM EXTRACT∙CITRUS JUNOS SEED EXTRACT∙ERIOBOTRYA JAPONICA LEAF EXTRACT∙ALUMINUM HYDROXIDE∙STEARIC ACID ISOSTEARIC ACID∙BUTYLENE GLYCOL∙TRISODIUM EDTA∙POLYESTER-1 ALCOHOL∙SILICA DIMETHYL SILYLATE∙ALUMINA∙TRIETHOXYCAPRYLYLSILANE HYDROGEN DIMETHICONE∙BHT∙TOCOPHEROL∙PHENOXYETHANOL∙BENZOIC ACID∙FRAGRANCE TITANIUM DIOXIDE IRON OXIDES MICA∙

Other Information

protect this product in this container from excessive heat and direct sun.

Questions or Comments?

Call toll free 1-800-906-7503

PRINCIPAL DISPLAY PANEL - 50 mL Tube Carton

WASO

SHISEIDO
GINZA TOKYO

COLOR-SMART
DAY MOISTURIZER
OIL-FREE
BROAD SPECTRUM
SPF 30
SUNSCREEN

50mL NET WT. 1.9 OZ.